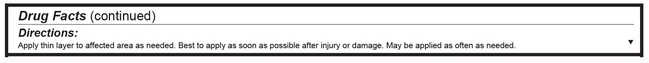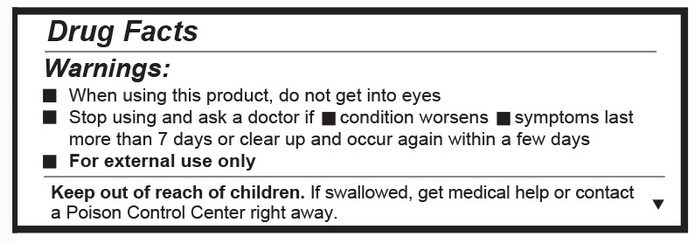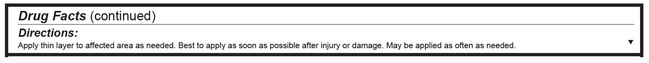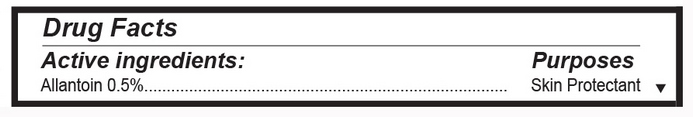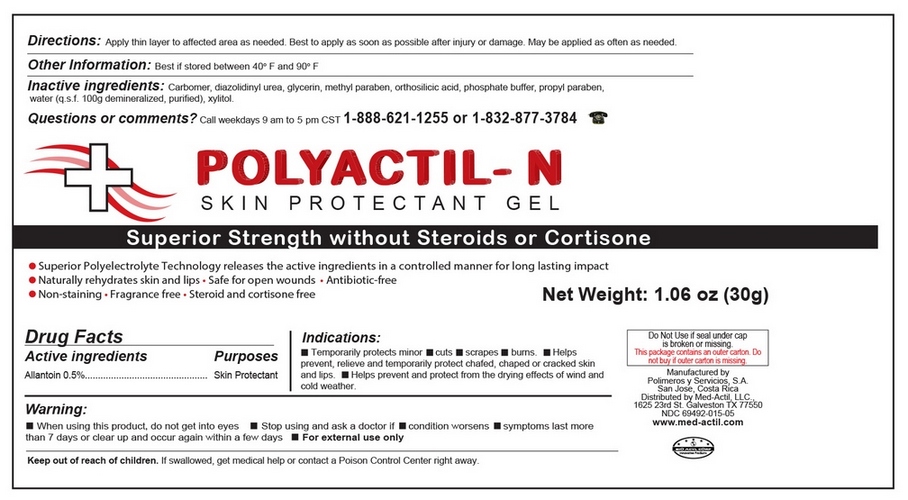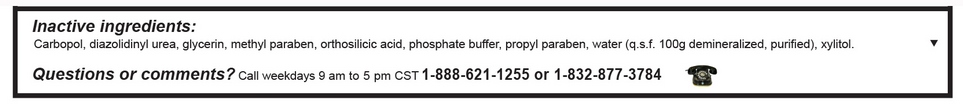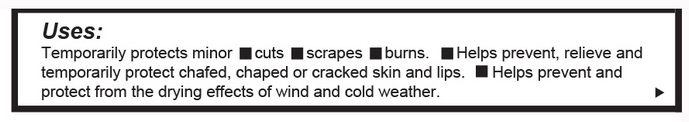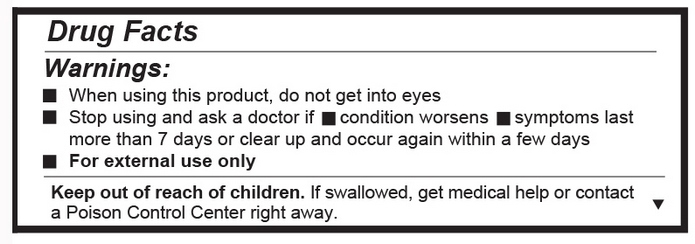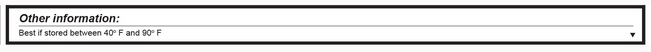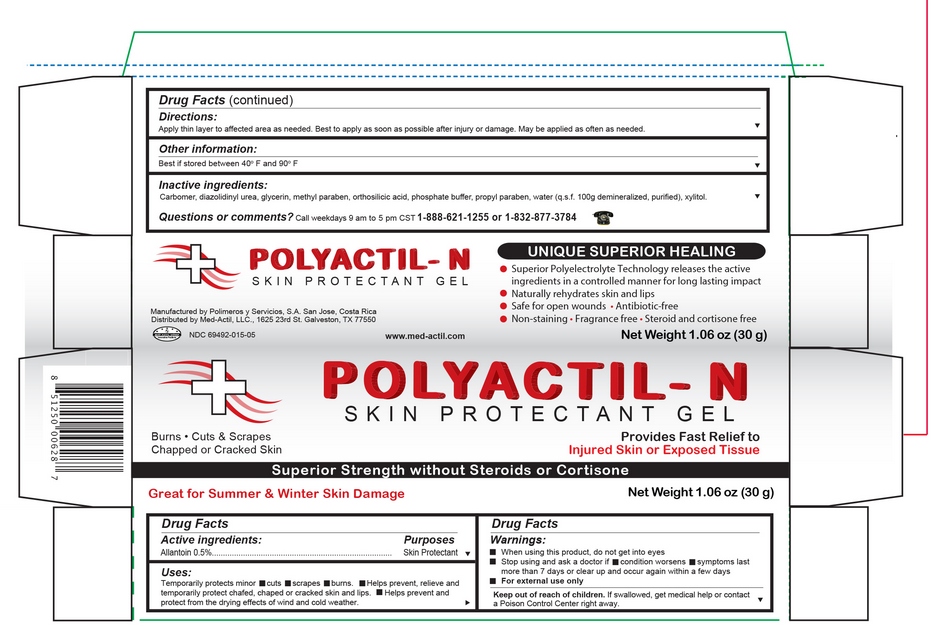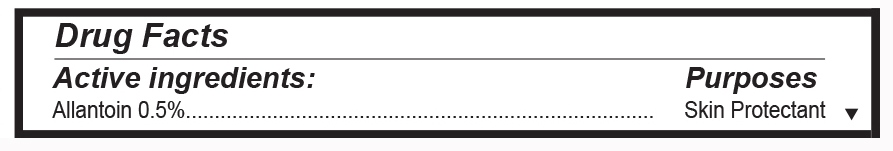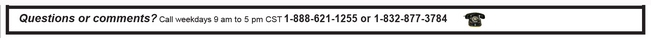 DRUG LABEL: Polyactil N
NDC: 69492-015 | Form: GEL
Manufacturer: POLIMEROS Y SERVICIOS S.A.
Category: otc | Type: HUMAN OTC DRUG LABEL
Date: 20190313

ACTIVE INGREDIENTS: ALLANTOIN 5 mg/1 g
INACTIVE INGREDIENTS: GLYCERIN; CARBOMER 940; ORTHOSILICIC ACID; SODIUM PHOSPHATE, DIBASIC; XYLITOL; DIAZOLIDINYL UREA; METHYLPARABEN; PROPYLPARABEN; WATER

Submission for Polyactil-N Skin Pritectant

Detail showing Active Ingredient from package

Information shown both on container label and paclage

Drug fact active ingredients -.jpg

Detail showing Inactive ingredient from package

Information shown both on cntainer label and package

Inactive ingredients-.jpg

Detail showing Purpose within Purposes from package

Information shown both on container label and package

Purpose .jpg

Detail showing Indications from pacage

Information shown both on container label and package

Indicationss.jpg

Detail shyowing Instructions for use and named Directions from package

Information shown both on container label and package

Drug Fast (continued).jpg

Detail showing Dosage abd Administration within Directions from package

Information shown both on container lable and package

Dosage and ad.jpg

Detail showing Warnings from package

Information shown both on container label and package

Drug Facts Warnings.jpg

Detail showing Keep Out of Reach of Children within Warnings from package

Information shown on package

Keep out of reach of chilfren.jpg

Detail showing Questions from package

Information shown on package

Questions or comments.jpg

Detail showing Other Safety Information from package

Information shown both on container label and package

Other informations-.jpg

Representative sample image of carton/container label

General view of inner container label

Etiqueta de Polyactil - N Lunes 20 06 16.jpg

General view of box content of labeling

Polyactil - N Lunes 20 06 16.jpg